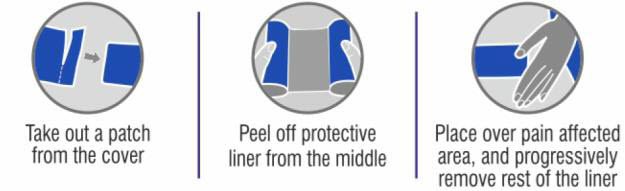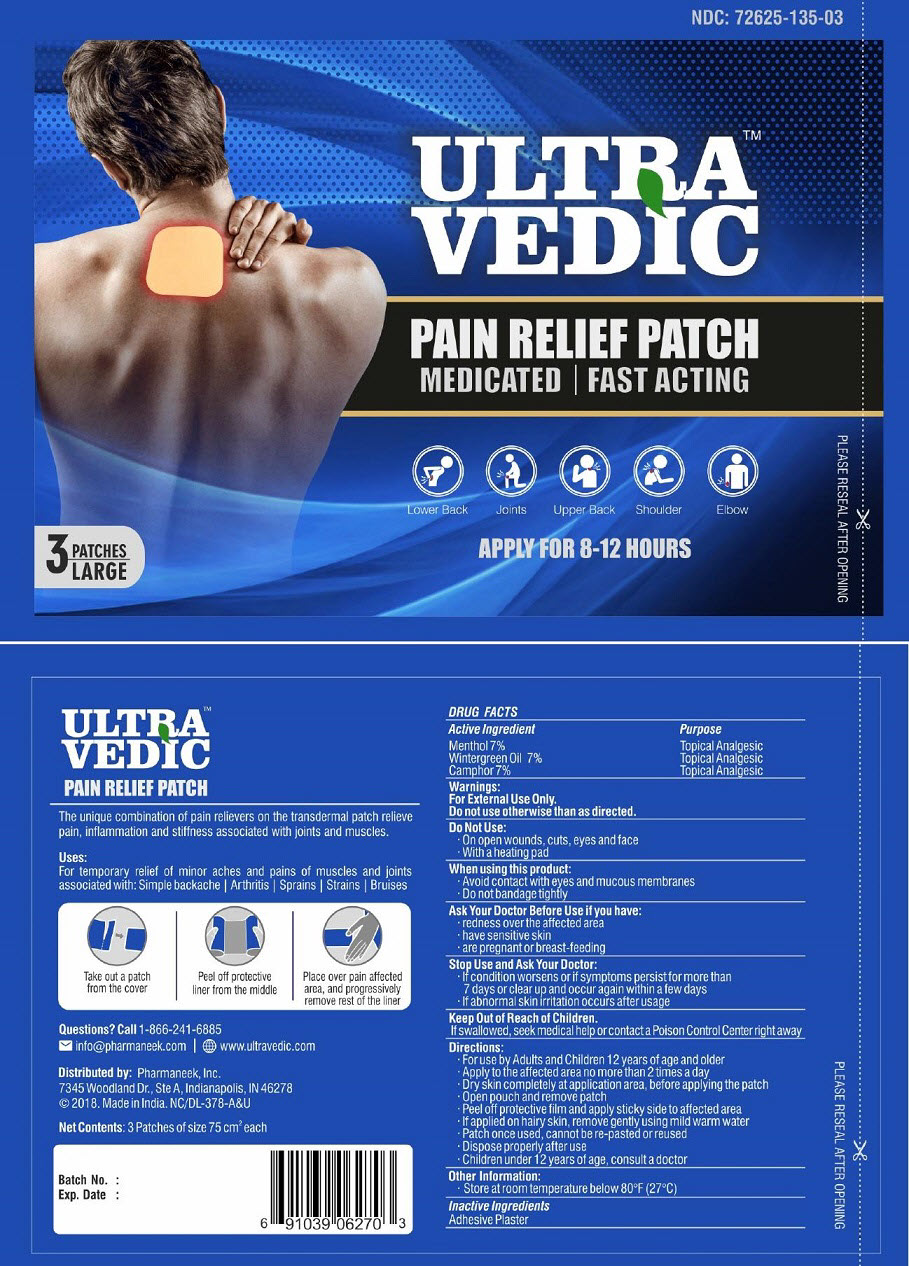 DRUG LABEL: Ultra Vedic
NDC: 72625-135 | Form: PATCH
Manufacturer: Pharmaneek, Inc.
Category: otc | Type: HUMAN OTC DRUG LABEL
Date: 20210120

ACTIVE INGREDIENTS: MENTHOL, UNSPECIFIED FORM 78.75 mg/1 1; METHYL SALICYLATE 78.75 mg/1 1; CAMPHOR (NATURAL) 78.75 mg/1 1
INACTIVE INGREDIENTS: MINERAL OIL

Ultra Vedic TM

Pain Relief Patch

The unique combination of pain relievers on the transdermal patch relieve pain, inflammation and stiffness associated with joints and muscles.

Active Ingredient

Menthol 10%

Wintergreen Oil 7%

Camphor 7%

Purpose

Topical Analgesic

Topical Analgesic

Topical Analgesic

Uses

For temporary relief of minor aches and pains of muscles and joints associated with: Simple backache | Arthritis | Sprains | Strains | Bruises.

Warnings

For External Use Only

Do not use otherwise than as directed.

Do Not Use

- On open wounds, cuts, eyes, and face
- With a heating pad

When using this product

- Avoid contact with eyes and mucous membranes
- Do not bandage tightly

Ask Your Doctor Before Use if you have

- redness over the affected area
- have sensitive skin
- are pregnant or breast-feeding

Stop Use and Ask Your Doctor

- If condition worsens or if symptoms persist for more than 7 days or clear up and occur again within a few days
- If abnormal skin irritation occurs after usage

KEEP OUT OF REACH OF CHILDREN

If swallowed, seek medical help or contact a Poison Control Center right away.

Directions

- For use by Adults and Children 12 year of age and older
- Apply to the affected area no more than 2 times a day
- Dry skin completely at application site area, before applying the patch
- Open pouch and remove patch
- Peel off protective film and apply sticky side to affected area
- If applied on hairy skin, remove gently using mild warm water
- Patch once used, cannot be re-pasted or reused
- Dispose properly after use
- Children under 12 years of age, consult a doctor

Other Information

- Store at room temperature below 80°F (27°C)

Inactive Ingredient

Adhesive Plaster

Questions?

Call 1-866-241-6885
info@pharmaneek.com
www.ultravedic.com

Distributed by:
Pharmaneek, Inc.
7345 Woodland Dr., Ste A,
Indianapolis, IN 46278
© 2018. Made in India. NC/DL-378-A&U

Net Contents: 3 Patches of size 75 cm^2 each

PACKAGE LABEL.PRINCIPAL DISPLAY PANEL

Please Reseal After Opening

NDC: 72625-135-03
ULTRA VEDICTM

Pain Relief Patch
Medicated | Fast Acting

Lower Back, Joints, Upper Back, Shoulder, Elbow
3 Large Patches
Apply for 8-12 Hours